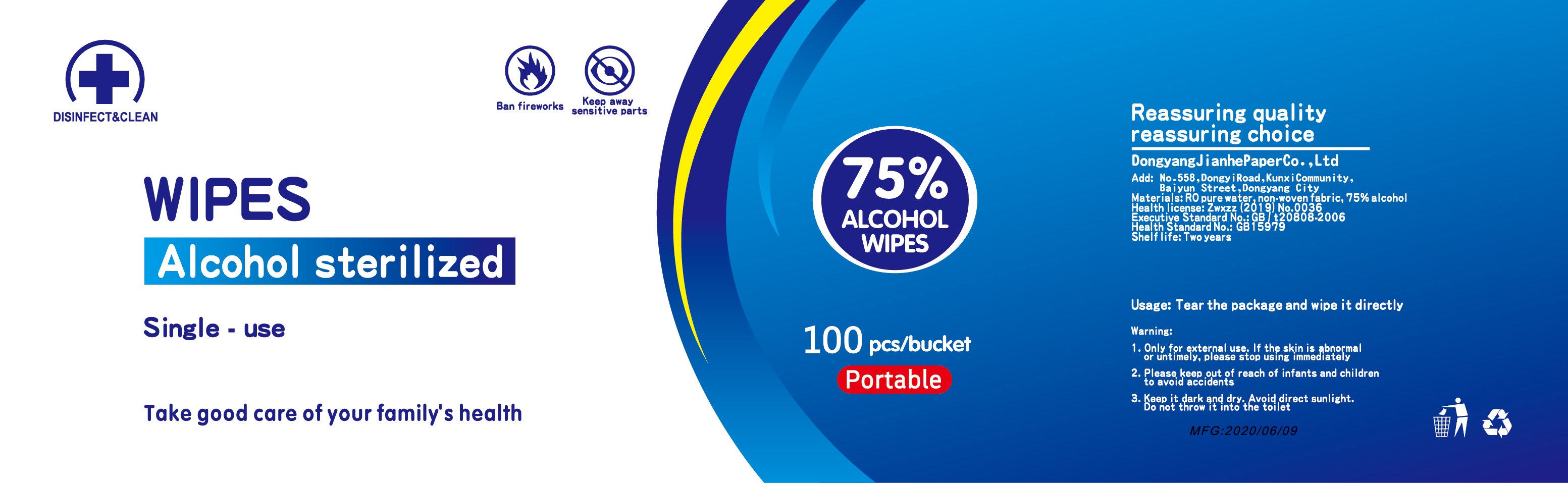 DRUG LABEL: RightCare Sanitizing  wipes
NDC: 58428-003 | Form: CLOTH
Manufacturer: OUTSOURCE PHARMACY SOLUTIONS INC.
Category: otc | Type: HUMAN OTC DRUG LABEL
Date: 20201013

ACTIVE INGREDIENTS: ALCOHOL 75 mL/100 1
INACTIVE INGREDIENTS: POLYESTER (ADIPIC ACID, 1,6-HEXANEDIOL, NEOPENTYL GLYCOL); ALOE; WATER; DIRECT BLACK 19

DOSAGE AND ADMINISTRATION

Keep it dark and dry. Avoid direct sunlight.

INACTIVE INGREDIENT

water,Polyester,Viscose, ALOE

INDICATIONS AND USAGE

Tear the package and wipe it directly.

ACTIVE INGREDIENT

Alcohol

KEEP OUT OF REACH OF CHILDREN

Please keep out of reach of infants and children to avoid accidents

PURPOSE

Disinfection
Sterilization
No Rinseing

WARNINGS

1. Only for external use. If the skin is abnormal or untimely, please stop using immediately
2. Please keep out of reach of infants and children to avoid accidents
3. Keep it dark and dry. Avoid direct sunlight.DO not throw it into the toilet